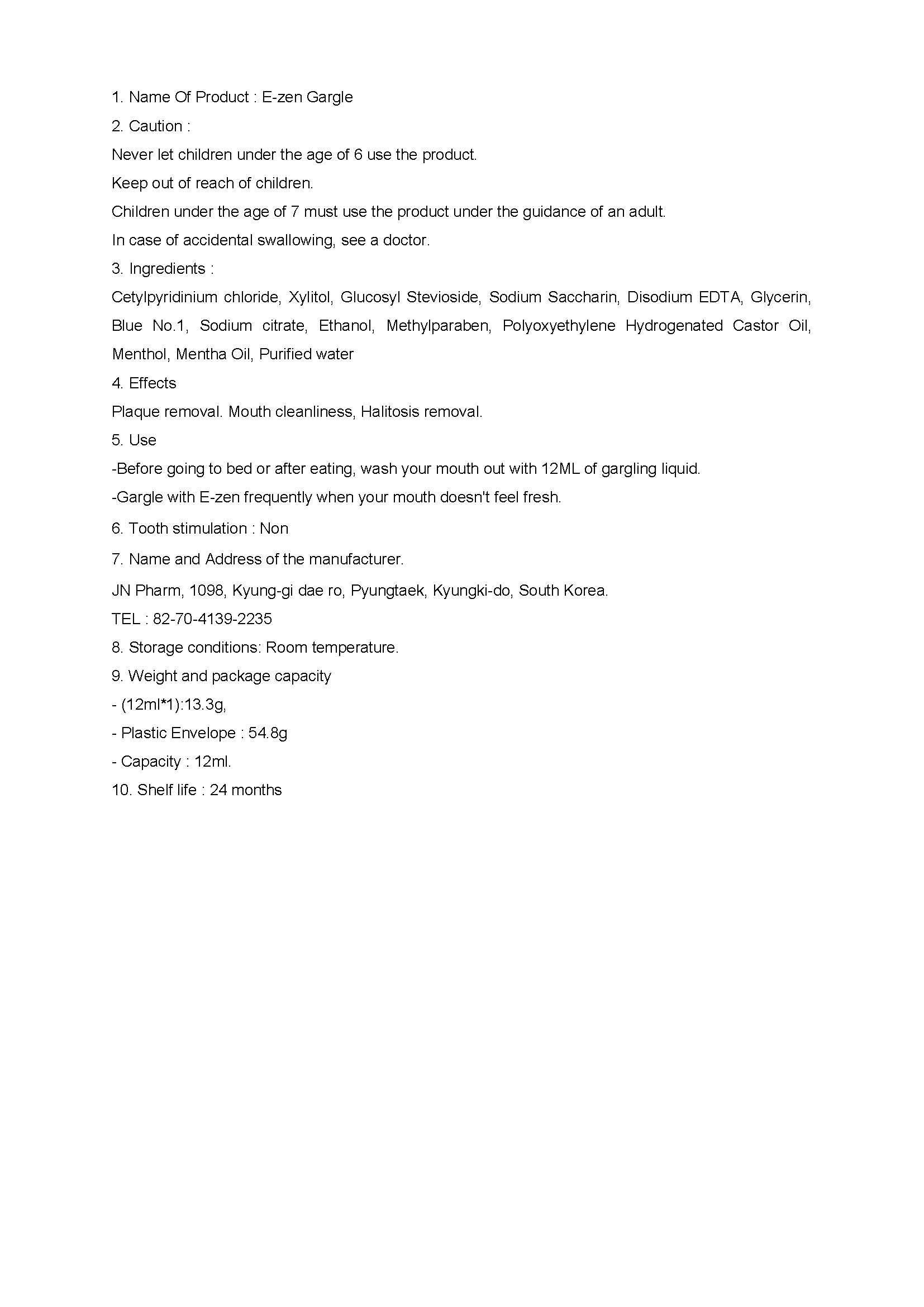 DRUG LABEL: E-zen Gargle
NDC: 62040-2001 | Form: LIQUID
Manufacturer: JN Pharm
Category: otc | Type: HUMAN OTC DRUG LABEL
Date: 20140208

ACTIVE INGREDIENTS: CETYLPYRIDINIUM CHLORIDE 0.005 g/100 mL
INACTIVE INGREDIENTS: WATER; GLYCERIN; XYLITOL; SODIUM CITRATE; METHYLPARABEN

Drug Facts

ACTIVE INGREDIENT

Cetylpyridinium chloride

INACTIVE INGREDIENT

Xylitol, Glucosyl Stevioside, Sodium Saccharin, Disodium EDTA, Glycerin, Blue No.1, Sodium citrate, Ethanol, Methylparaben, Polyoxyethylene Hydrogenated Castor Oil, Menthol, Mentha Oil, Purified water

PURPOSE

Plaque removal. Mouth cleanliness, Halitosis removal

keep out or reach of the children

INDICATIONS AND USAGE

-Before going to bed or after eating, wash your mouth out with 12ML of gargling liquid.-Gargle with E-zen frequently when your mouth doesn't feel fresh.

WARNINGS

Never let children under the age of 6 use the product.Keep out of reach of children.Children under the age of 7 must use the product under the guidance of an adult.In case of accidental swallowing, see a doctor.

DOSAGE AND ADMINISTRATION

dental use only